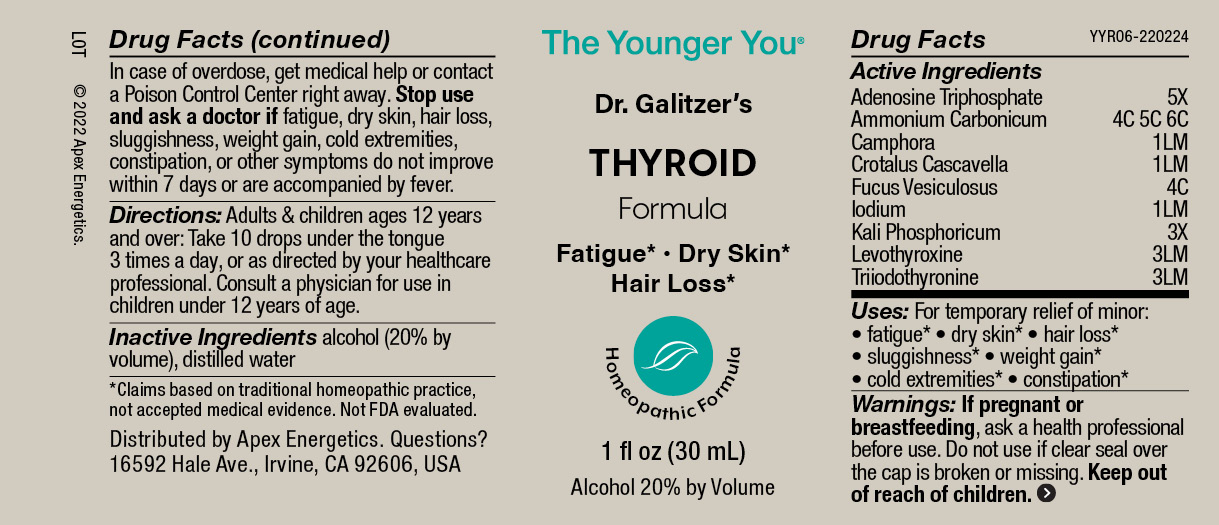 DRUG LABEL: THYROID Formula
NDC: 63479-2506 | Form: SOLUTION/ DROPS
Manufacturer: Apex Energetics Inc.
Category: homeopathic | Type: HUMAN OTC DRUG LABEL
Date: 20240108

ACTIVE INGREDIENTS: AMMONIUM CARBONATE 6 [hp_C]/1 mL; LEVOTHYROXINE 3 [hp_Q]/1 mL; CROTALUS DURISSUS TERRIFICUS VENOM 1 [hp_Q]/1 mL; FUCUS VESICULOSUS 4 [hp_C]/1 mL; CAMPHOR (NATURAL) 1 [hp_Q]/1 mL; LIOTHYRONINE 3 [hp_Q]/1 mL; ADENOSINE TRIPHOSPHATE 5 [hp_X]/1 mL; IODINE 1 [hp_Q]/1 mL; DIBASIC POTASSIUM PHOSPHATE 3 [hp_X]/1 mL
INACTIVE INGREDIENTS: WATER; ALCOHOL

YYR06

Active Ingredients
Adenosine Triphosphate Ammonium Carbonicum Camphora Crotalus Cascavella Fucus Vesiculosus Iodium Kali Phosphoricum Levothyroxine Triiodothyronine | 5X 4C 5C 6C 1LM 1LM 4C 1LM 3X 3LM 3LM

Uses:

PURPOSE

For temporary relief of minor:

fatigue*

dry skin*

hair loss*
sluggishness*

weight gain*

cold extremities*

constipation*

Warnings:

PREGNANCY OR BREAST FEEDING

If pregnant or breastfeeding, ask a health professional before use.

Do not use if clear seal over the cap is broken or missing.

Keep out of reach of children.In case of overdose, get medical help or contact a Poison Control Center right away.

Stop use and ask a doctor if fatigue, dry skin, hair loss, sluggishness, weight gain, cold extremities, constipation, or other symptoms do not improve within 7 days or are accompanied by fever

Directions:

Adults & children ages 12 years and over: Take 10 drops under the tongue 3 times a day, or as directed by your healthcare professional.

Consult a physician for use in children under 12 years of age

Inactive Ingredients

alcohol (20% by volume), distilled water

Distributed by Apex Energetics. Questions?

16592 Hale Ave., Irvine, CA 92606, USA

PACKAGE LABEL

The Younger You®

Dr. Galitzer’s

THYROID

Formula

Fatigue* •Dry Skin*

Hair Loss*

Homeopathic Formula

1 FL OZ (30 mL)

Alcohol 20% by Volume